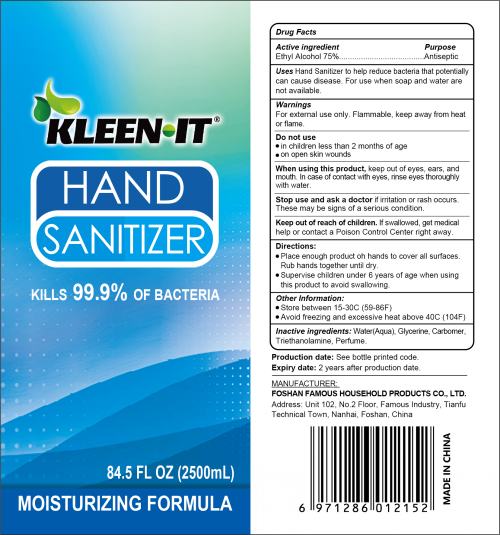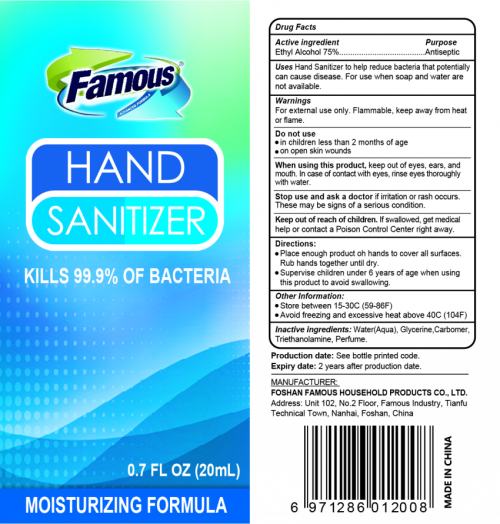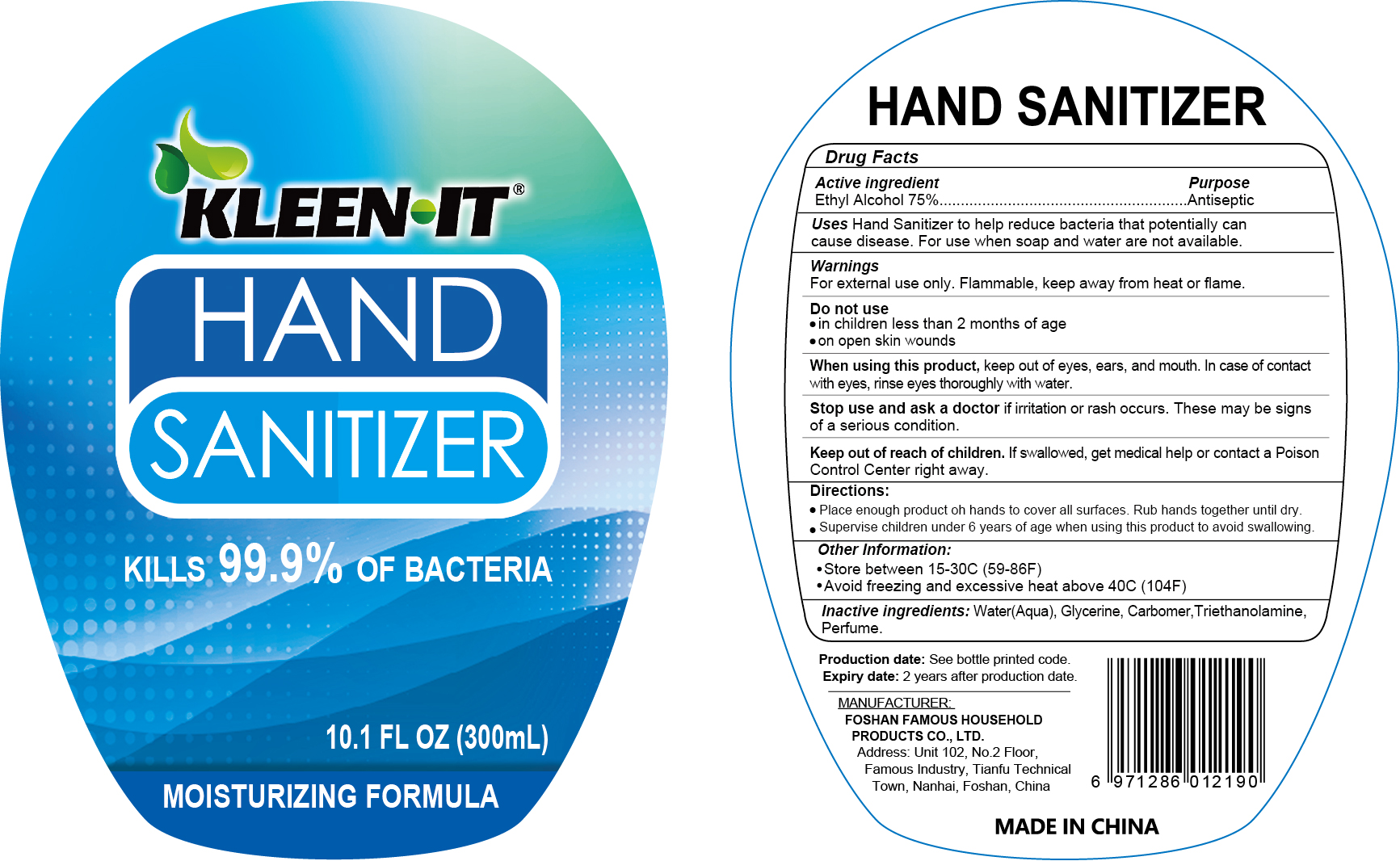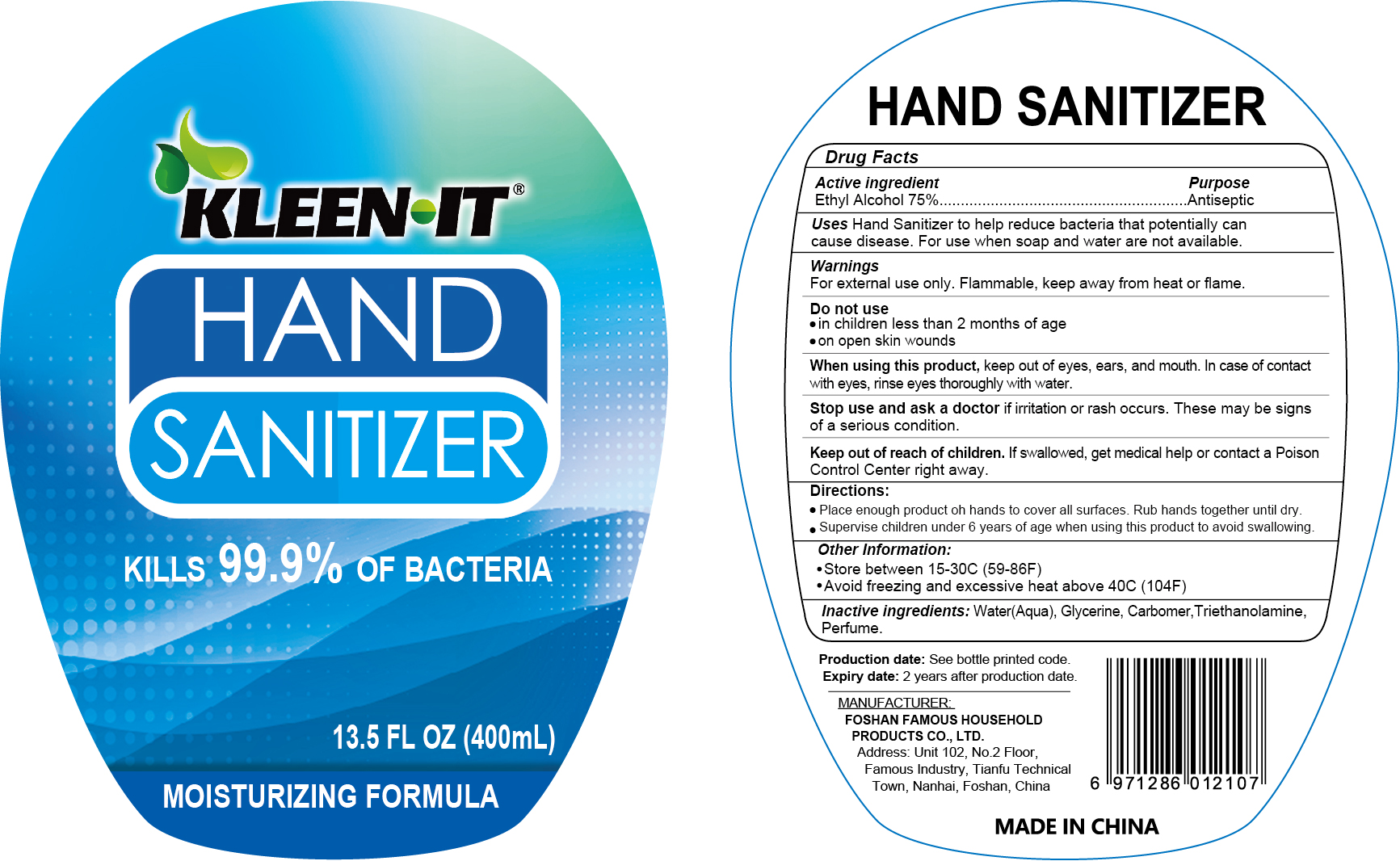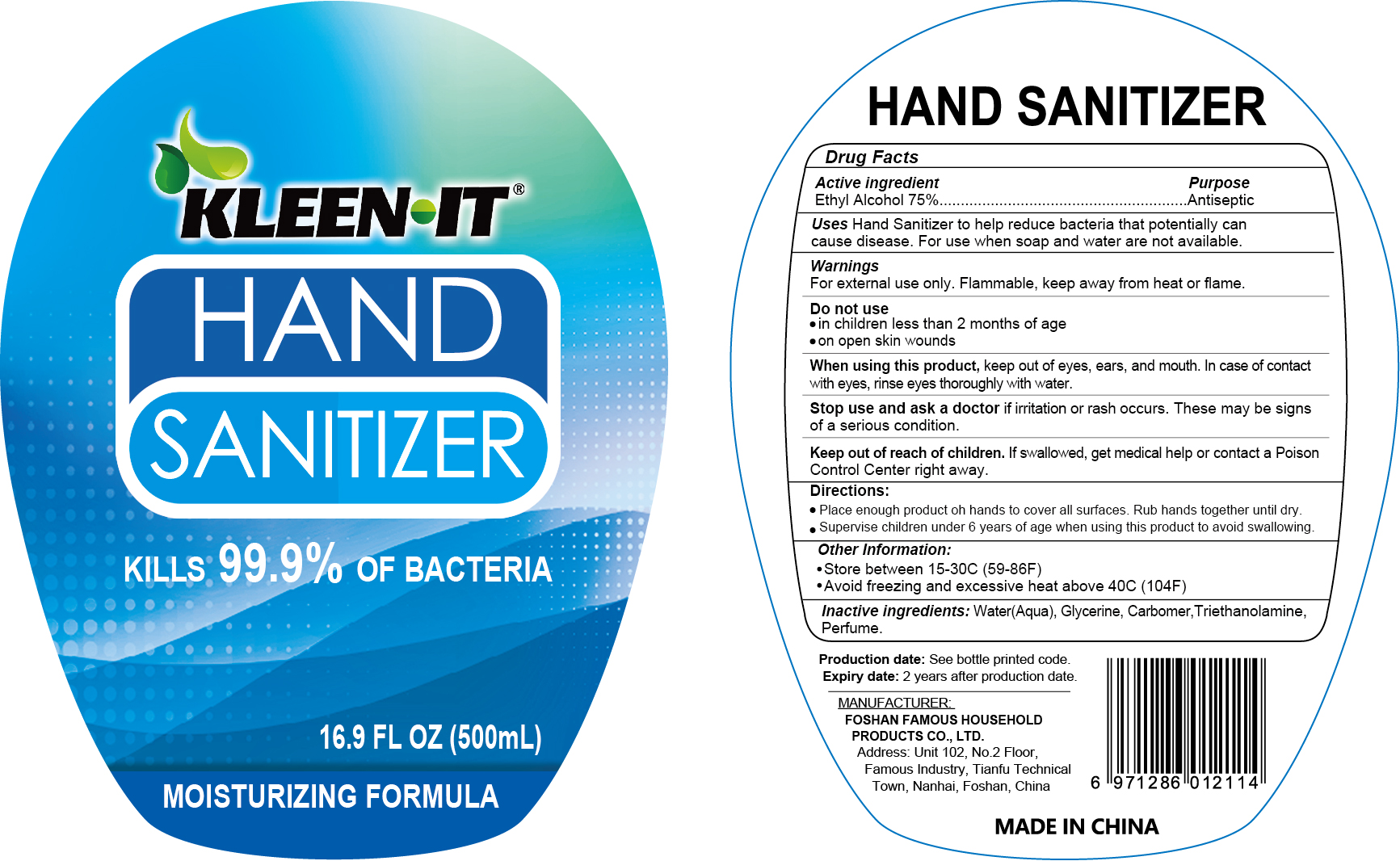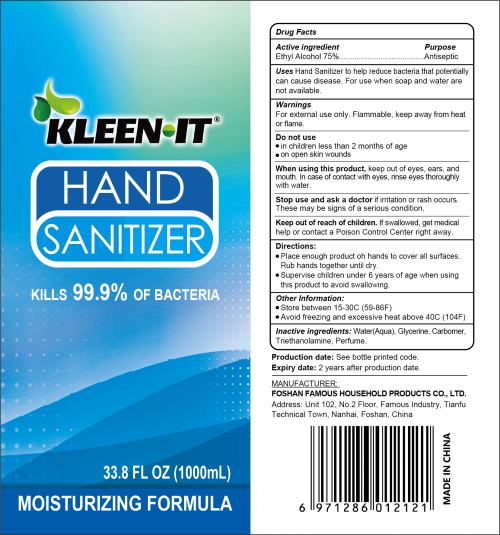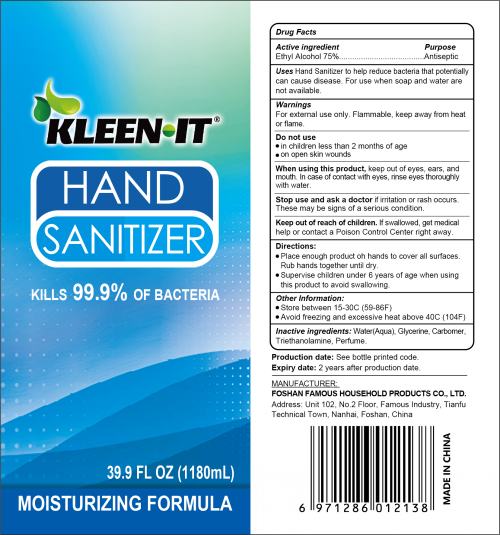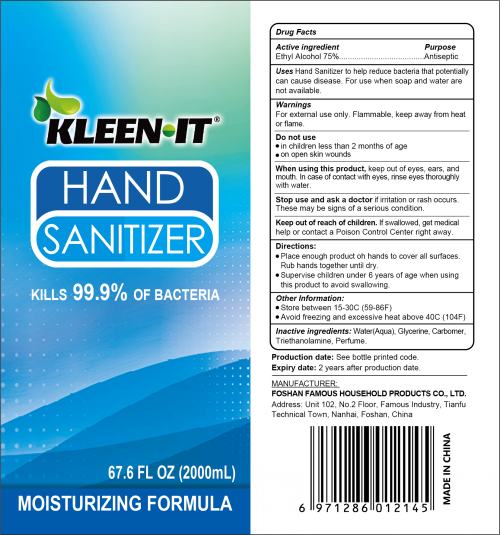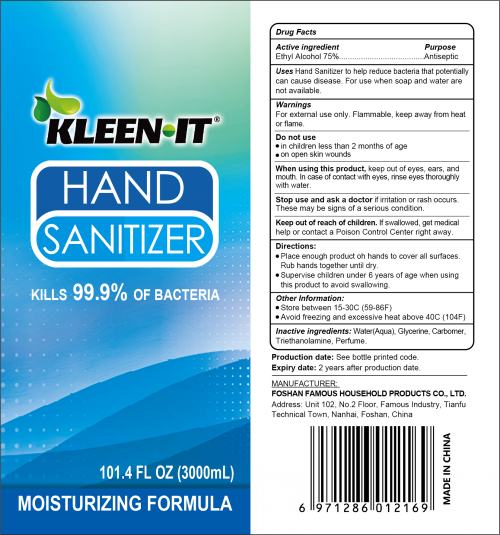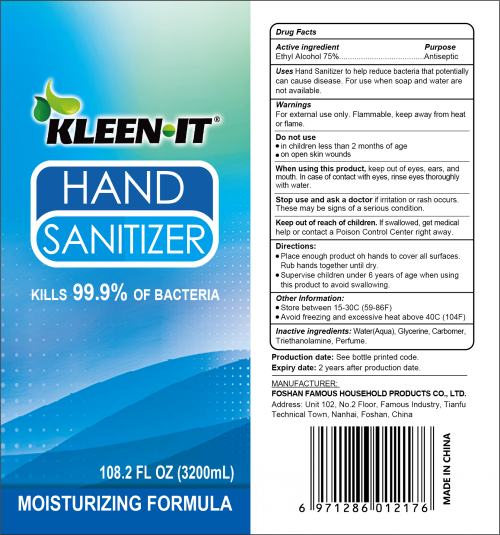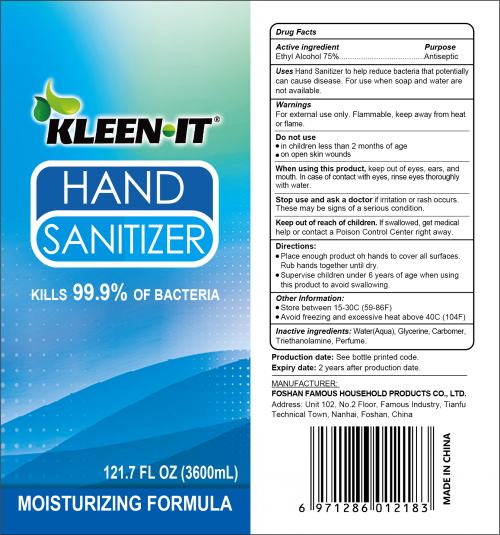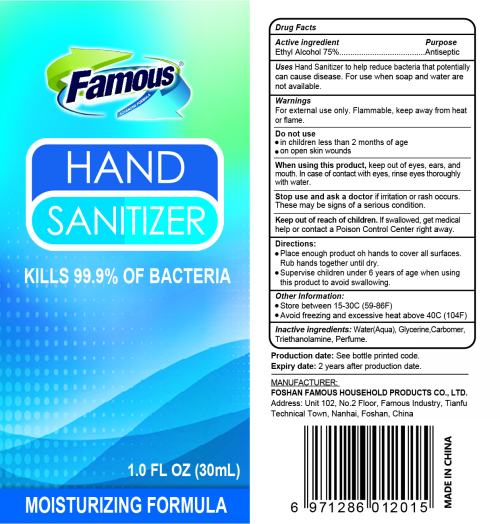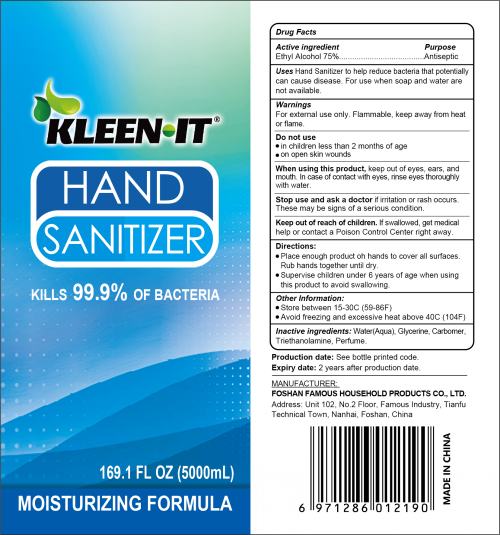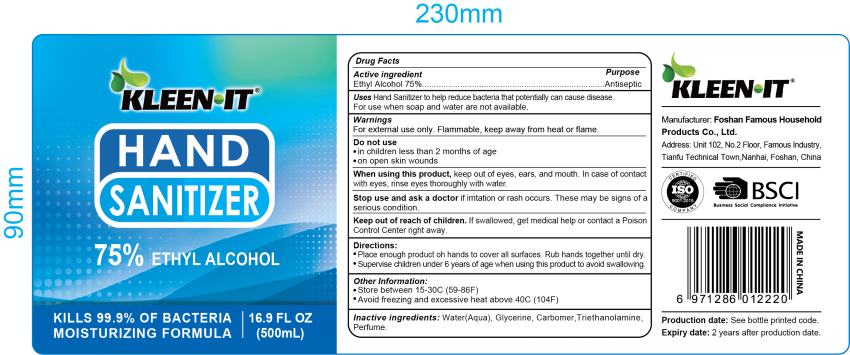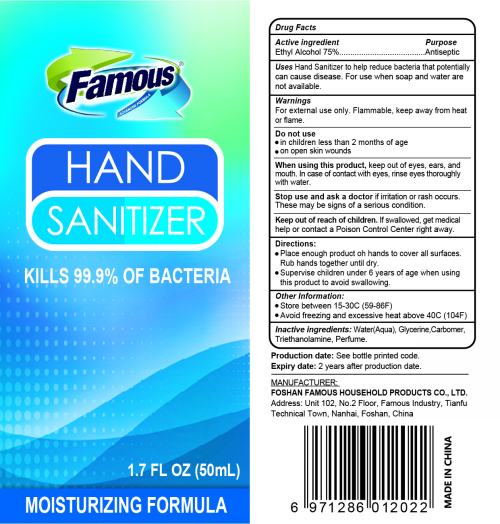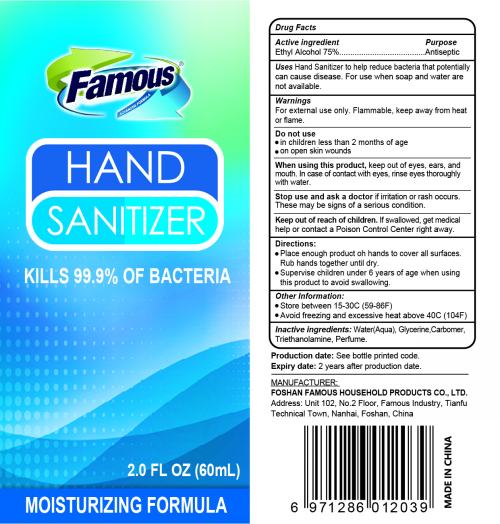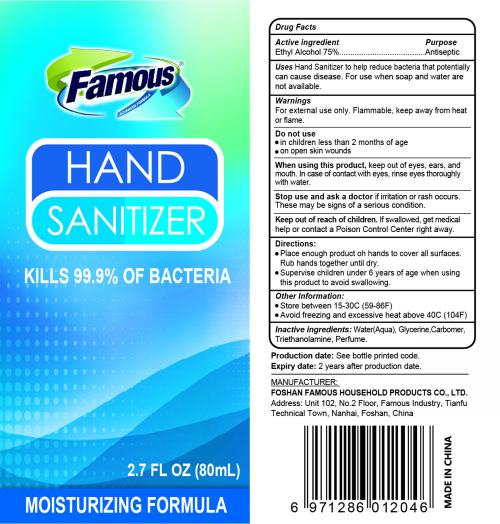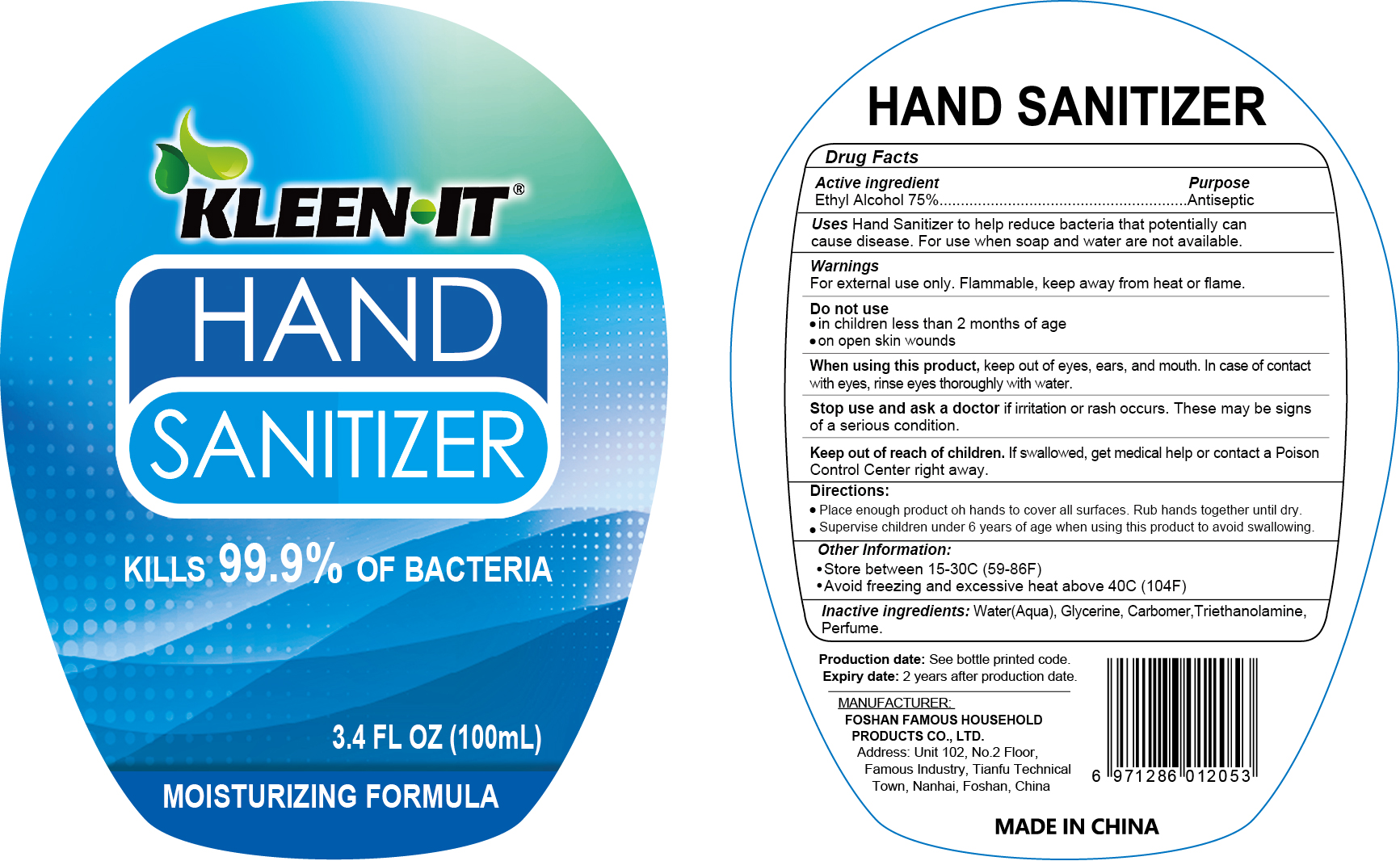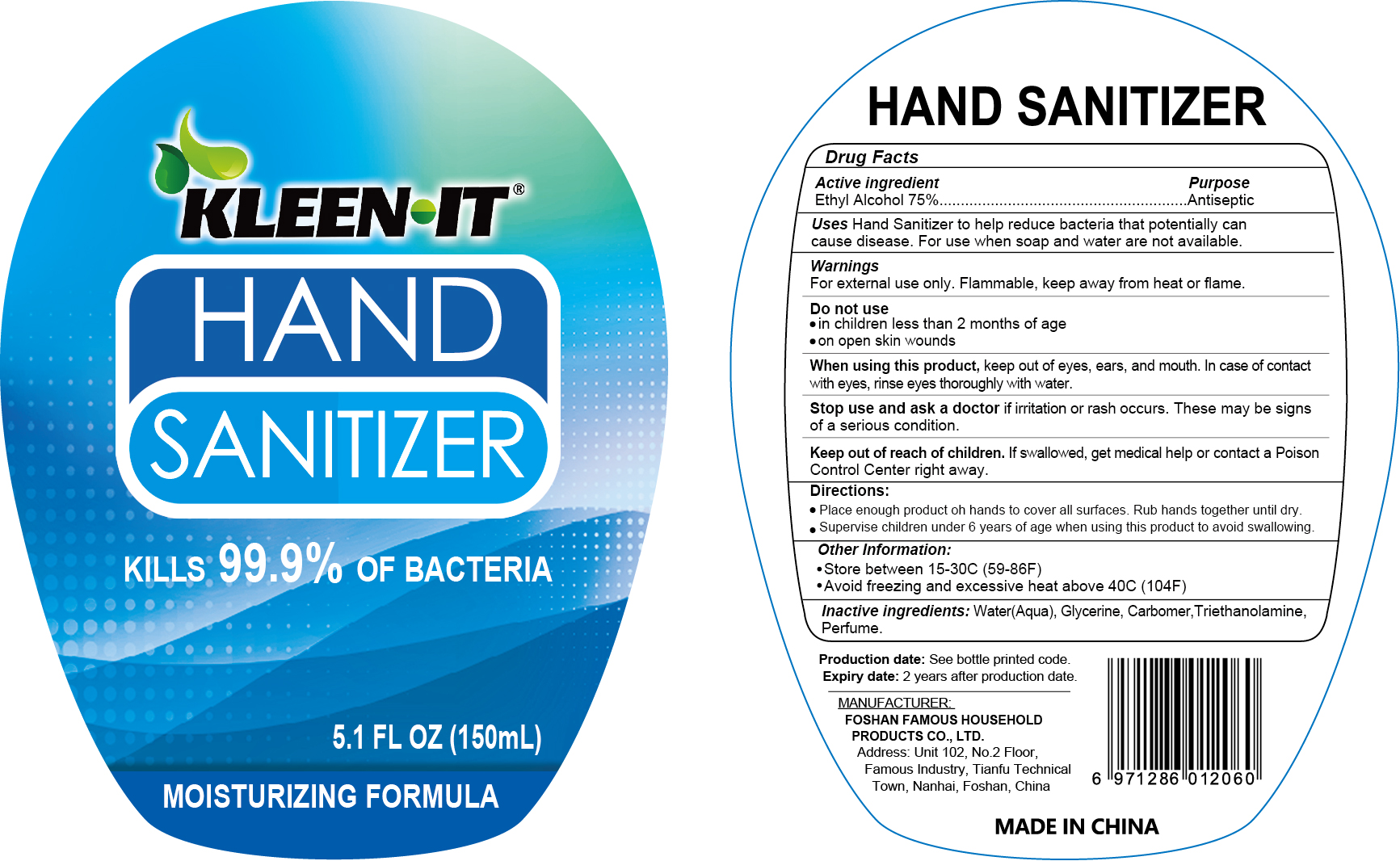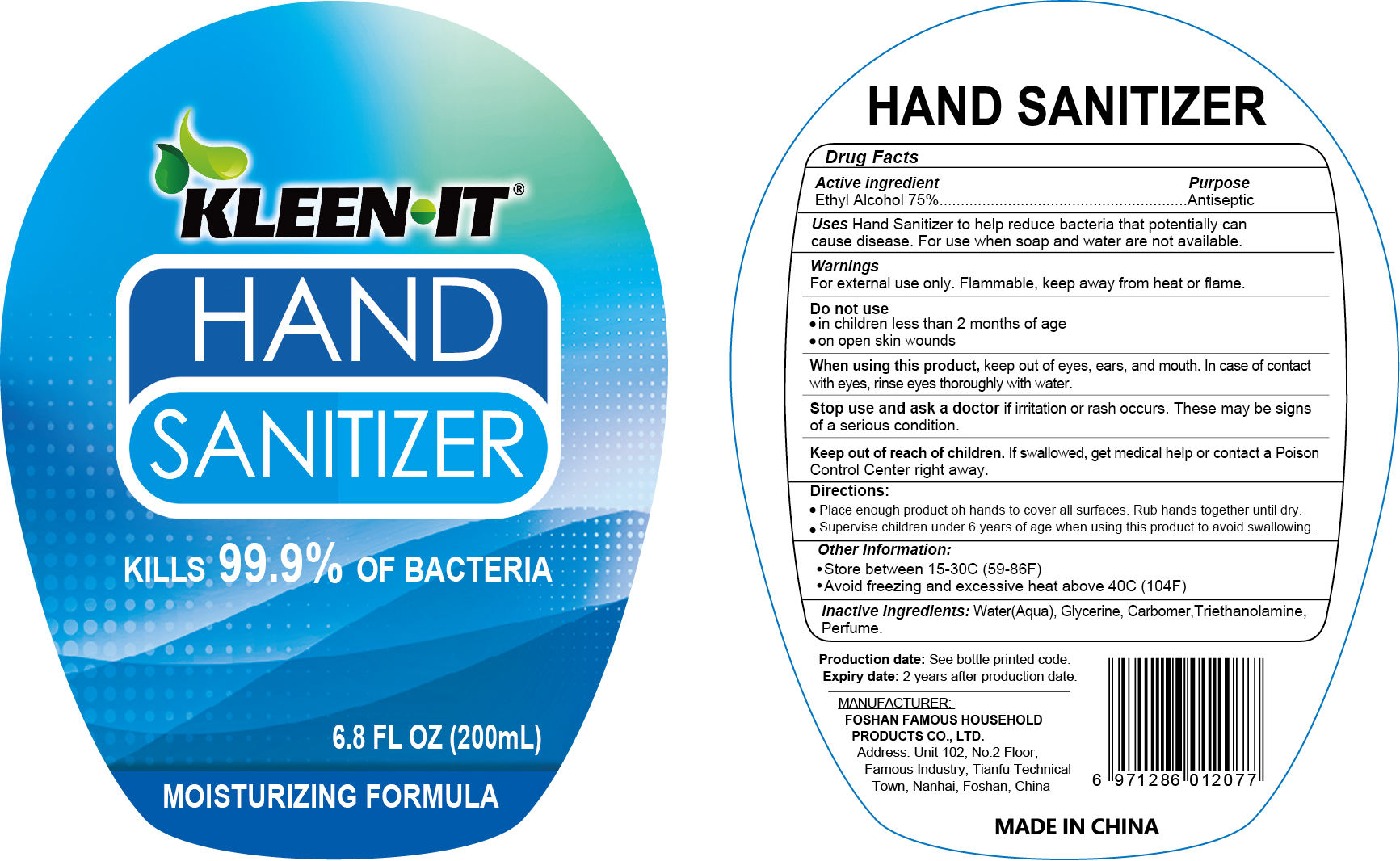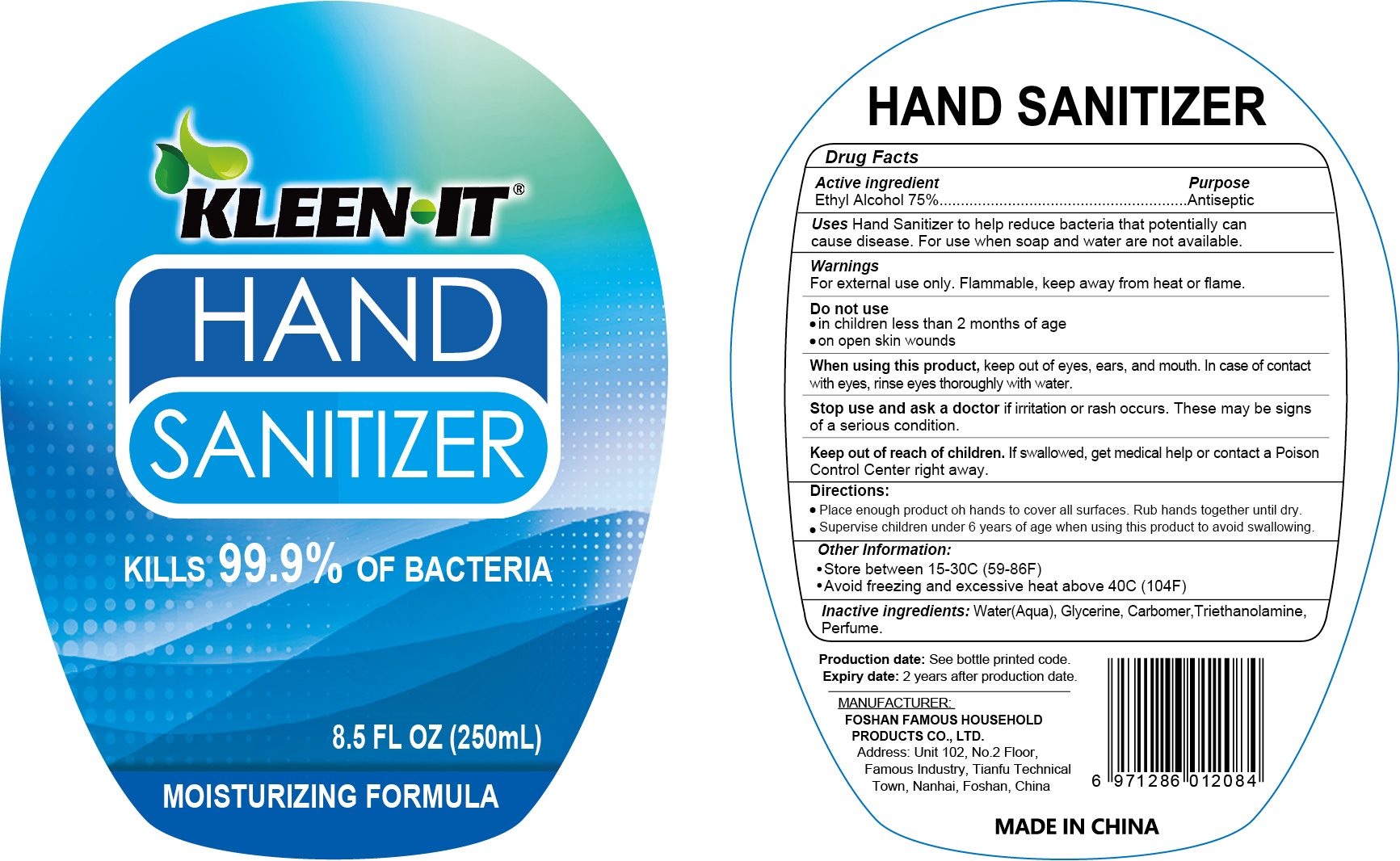 DRUG LABEL: Hand Sanitizer
NDC: 75265-001 | Form: GEL
Manufacturer: Foshan Famous Household Products Co., Ltd
Category: otc | Type: HUMAN OTC DRUG LABEL
Date: 20220215

ACTIVE INGREDIENTS: ALCOHOL 75 mL/100 mL
INACTIVE INGREDIENTS: CARBOMER HOMOPOLYMER, UNSPECIFIED TYPE; TROLAMINE; WATER; GLYCERIN

Hand Sanitizer

Active ingredient

Ethyl Alcohol 75%

Purpose

Antiseptic

Uses

Hand Sanitizer to help reduce bacteria that potentially can cause disease.For use when soap and water are not available.

Warnings

For external use only.Flammable, keep away from heat or fiame.

Do not use

in children less than 2 months of age

on open skin wounds

When using this product

keep out of eyes,ears, and mouth.In case of contact with eyes,rinse eyes thoroughly with water.

Stop use and ask a doctor if irritation or rash occurs. These may be signs of a serious condition.

Keep out of reach of children

If swallowed,get medical help or contact a Poison Control Center right away.

Directions

Place enough product oh hands to cover all surfaces.

Rub hands together until dry.

Supervise children under 6 years of age when using this product to avoid swallowing.

Other Information

Store between 15-30C(59-86F)

Avoid freezing and excessive heat above 40C(104F)

Inactive ingredients

Water(Aqua),Glycerine,Carbomer,Triethanolamine,Perfume.